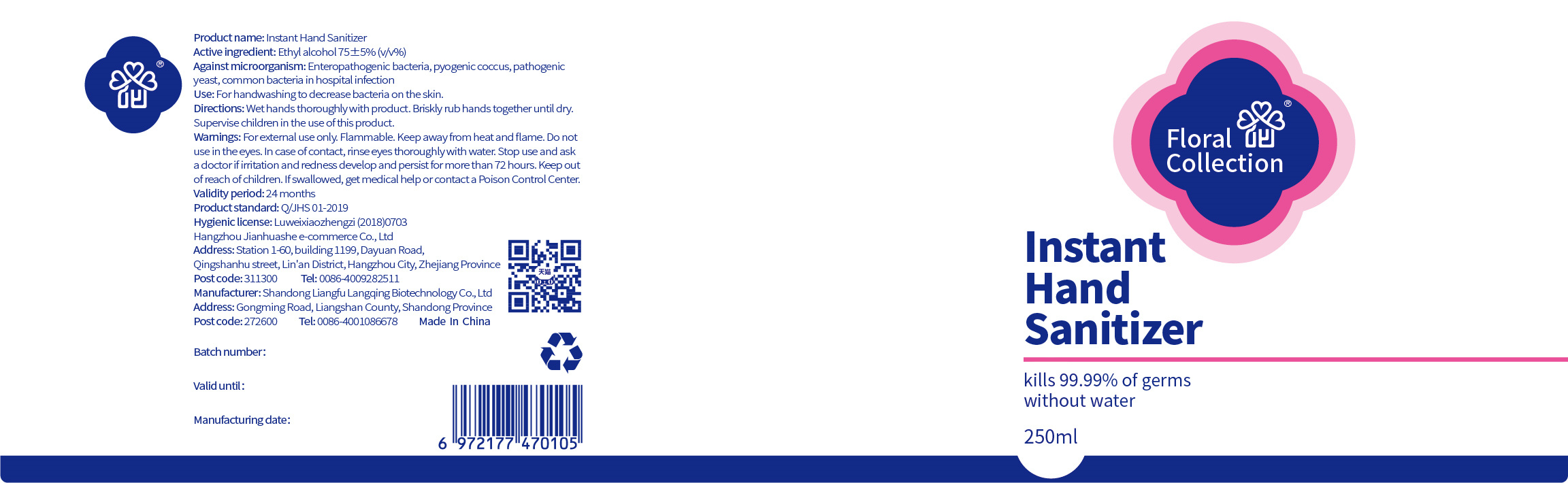 DRUG LABEL: Instant Hand Sanitizer
NDC: 41979-004 | Form: LIQUID
Manufacturer: Shandong Liangfu Langqing Biological Technology Co., Ltd.
Category: otc | Type: HUMAN OTC DRUG LABEL
Date: 20200506

ACTIVE INGREDIENTS: ALCOHOL 187.5 mL/250 mL
INACTIVE INGREDIENTS: CARBOMER COPOLYMER TYPE A (ALLYL PENTAERYTHRITOL CROSSLINKED); GLYCERETH-26; PHENOXYETHANOL; WATER; TROLAMINE

Do not use in the eyes. In case of contact, rinse eyes thoroughly with water.

Stop use and ask a doctor if irritation and redness develop and persist for more than 72 hours.

Keep out of reach of children. If swallowed, get medical help or contact a Poison Control Center.

ACTIVE INGREDIENT

alcohol

INACTIVE INGREDIENT

water CARBOMER COPOLYMER TYPE A (ALLYL PENTAERYTHRITOL CROSSLINKED) GLYCERETH-26 PHENOXYETHANOL

TROLAMINE

INDICATIONS AND USAGE

Wet hands thoroughly with product.

Briskly rub hands together until dry.

Supervise children in the use of this product.

keep out of reach of children

DOSAGE AND ADMINISTRATION

Flammable. Keep away from heat and flame.

PURPOSE

Disinfection
Sterilization
No Rinseing